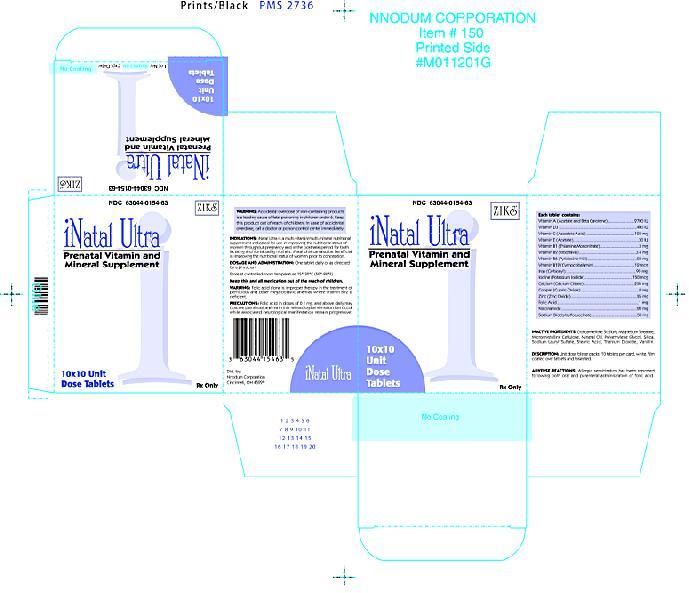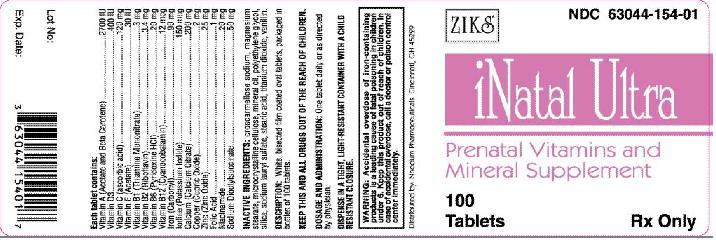 DRUG LABEL: INATAL Ultra
NDC: 63044-154 | Form: TABLET, COATED
Manufacturer: Nnodum Pharmaceuticals
Category: prescription | Type: HUMAN PRESCRIPTION DRUG LABEL
Date: 20091026

ACTIVE INGREDIENTS: VITAMIN A 2700 [iU]/1 1; ASCORBIC ACID 120 mg/1 1; CALCIUM CITRATE 200 mg/1 1; IRON PENTACARBONYL 90 mg/1 1; CHOLECALCIFEROL 400 [iU]/1 1; ALPHA-TOCOPHEROL ACETATE 30 [iU]/1 1; THIAMINE MONONITRATE 3 mg/1 1; RIBOFLAVIN 3.4 mg/1 1; NIACINAMIDE 20 mg/1 1; PYRIDOXINE HYDROCHLORIDE 20 mg/1 1; FOLIC ACID 1 mg/1 1; CYANOCOBALAMIN 12 ug/1 1; POTASSIUM IODIDE 150 ug/1 1; ZINC OXIDE 25 mg/1 1; CUPRIC OXIDE 2 mg/1 1; DOCUSATE SODIUM 50 mg/1 1
INACTIVE INGREDIENTS: CROSCARMELLOSE SODIUM; MAGNESIUM STEARATE; POLYETHYLENE GLYCOL; CELLULOSE, MICROCRYSTALLINE; MINERAL OIL; SODIUM LAURYL SULFATE; STEARIC ACID; TITANIUM DIOXIDE; VANILLIN

INATAL Ultra

Prenatal Multivitamin/
Multimineral Tablets
63044-154-63

Rx Only

WARNING: Accidental overdose of iron-containing prod-Ucts is a leading cause of fatal poisoning in children under 6. Keep this product out of the reach of children. In case of accidental overdose, call a doctor or poison control center immediately.

DESCRIPTION:

INATAL Ultra is a white, dye free, oval oil-and-water-soluble multivitamin/multimineral tablet with calcium citrate and carbonyl iron.

Each tablet contains:

Vitamin A* . . . . . . . . . . . . . . . . . . . . . . . 2700 I.U.

Vitamin C (Ascorbic Acid) . . . . . . . . . . . . . . 120 mg

Calcium (Calcium Citrate) . . . . . . . . . . . . . 200 mg

Elemental Iron (Carbonyl Iron) . . . . . . . . . . . 90 mg

Vitamin D3 (Cholecalciferol) . . . . . . . . . . . . 400 I.U.

Vitamin E (dl-Alpha Tocopheryl Acetate) . . . . . 30 I.U.

Vitamin B1 (Thiamine Mononitrate) . . . . . . . . . 3 mg

Vitamin B2 (Riboflavin) . . . . . . . . . . . . . . . . 3.4 mg

Niacinamide . . . . . . . . . . . . . . . . . . . . . . . . 20 mg

Vitamin B6 (Pyridoxine HCI) . . . . . . . . . . . . . 20 mg

Folic Acid . . . . . . . . . . . . . . . . . . . . . . . . . . . 1 mg

Vitamin B12 (Cyanocobalamin) . . . . . . . . . . 12 mcg

Iodine (Potassium Iodide) . . . . . . . . . . . . . 150 mcg

Zinc (Zinc Oxide) . . . . . . . . . . . . . . . . . . . . . 25 mg

Copper (Cupric Oxide) . . . . . . . . . . . . . . . . . 2 mg

Docusate Sodium . . . . . . . . . . . . . . . . . . . . 50 mg

*Input as Vitamin A palmitate and beta carotene.

INDICATIONS:

INATAL Ultra ® is a multivitamin/multimineral nutritional supplement indicated for use in improving the nutritional status of women throughout pregnancy and in the postnatal period for both lactating and nonlactating mothers. Ultra NatalCare® can also be beneficial in improving the nutritional status of women prior to conception.

CONTRAINDICATIONS:

This product is contraindicated in patients with a known hypersensitivity to any of the ingredients.

WARNINGS:

Folic Acid alone is improper therapy in the treatment of pernicious anemia and other megaloblastic anemias where vitamin B12 is deficient.

NOTICE: Contact with moisture may produce surface discoloration or erosion of the tablet.

PRECAUTIONS:

Folic acid in doses above 0.1 mg daily may obscure pernicious anemia in that hematologic remission can occur while neurological manifestations progress.

ADVERSE REACTIONS:

Allergic sensitization has been reported following both oral and parenteral administration of folic acid.

PEDIATRIC USE:

Safety and effectiveness in pediatric patients have not been established.

GERIATRIC USE:

Clinical studies on this product have not been performed in sufficient numbers of subjects aged 65 and over to determine whether elderly subjects respond differently from younger subjects. In general, dose selection for an elderly patient should be cautious, usually starting at the low end of the dosing range, reflecting the greater frequency of decreased hepatic, renal or cardiac function, and of concomitant disease or other drug therapy.

DOSAGE AND ADMINISTRATION:

One tablet daily or as directed by a physician.

HOW SUPPLIED:

NDC 63044-154-63 Unit Dose Packs containing 10 tablets per card.

Store at controlled room temperature 15°-30°C (59°-86°F).

KEEP THIS AND ALL DRUGS OUT OF THE REACH OF CHILDREN.

Manufactured for
Nnodum Pharmaceutical
Cincinnati, Ohio 45229